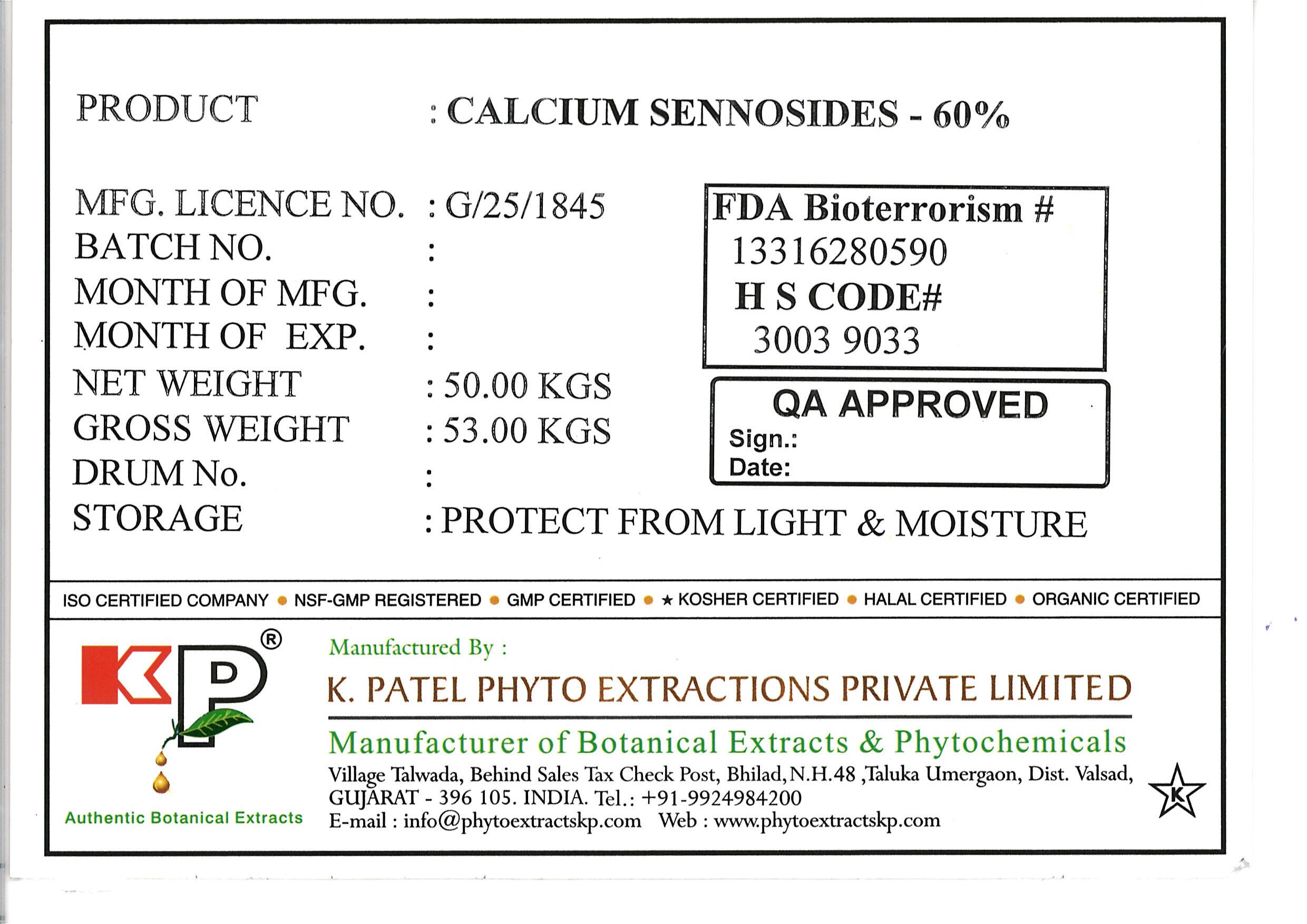 DRUG LABEL: Calcium Sennosides
NDC: 73276-002 | Form: POWDER
Manufacturer: K. Patel Phyto Extractions Private Limited
Category: other | Type: BULK INGREDIENT
Date: 20230110

ACTIVE INGREDIENTS: SENNOSIDES 50 kg/50 kg

Calcium Sennosides 60%